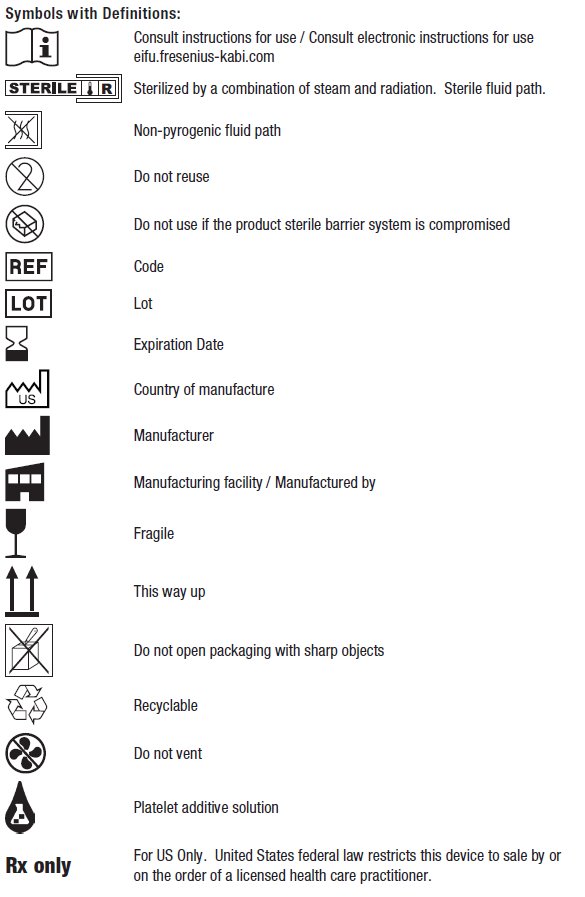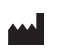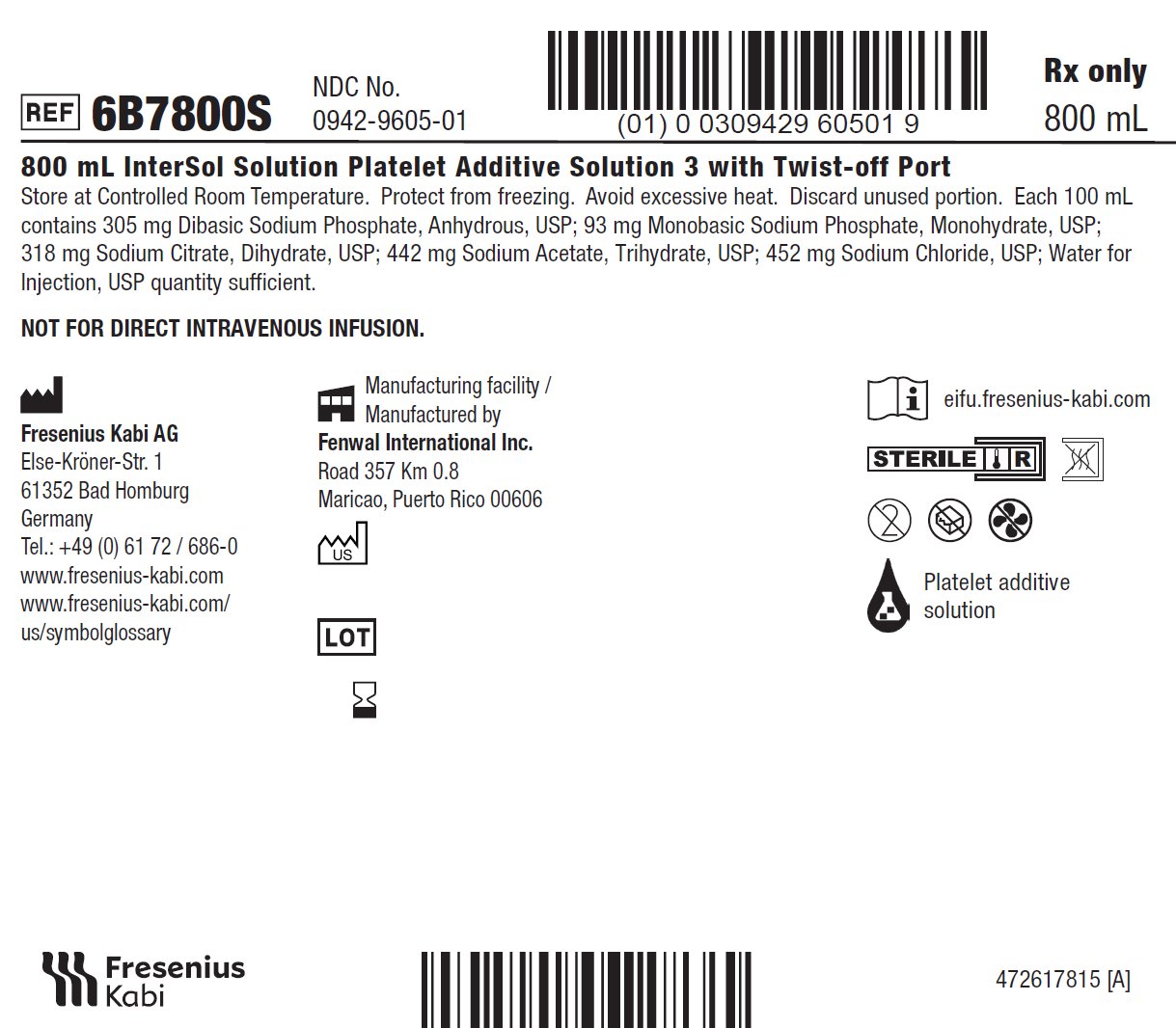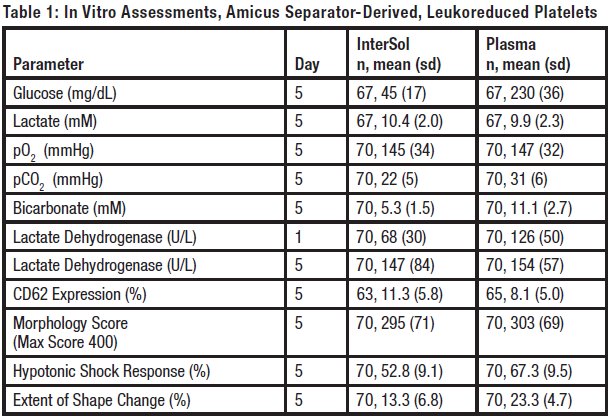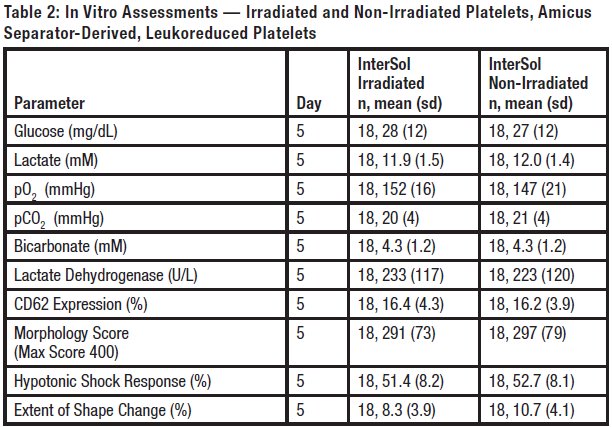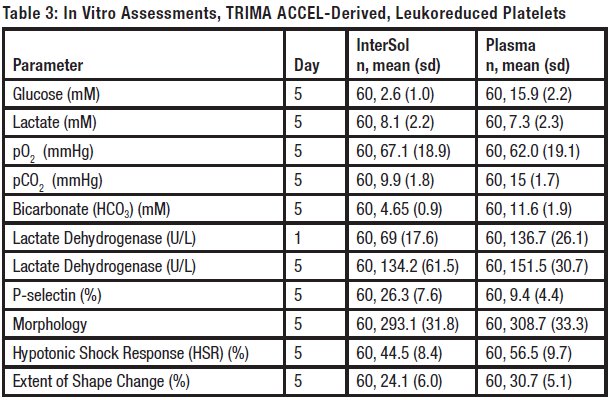 DRUG LABEL: InterSol
NDC: 0942-9605 | Form: SOLUTION
Manufacturer: Fenwal, Inc.
Category: prescription | Type: HUMAN PRESCRIPTION DRUG LABEL
Date: 20250627

ACTIVE INGREDIENTS: Sodium Chloride 452 mg/100 mL; SODIUM ACETATE 442 mg/100 mL; Trisodium Citrate Dihydrate 318 mg/100 mL; Sodium Phosphate, Monobasic, Monohydrate 93 mg/100 mL; SODIUM PHOSPHATE, DIBASIC, UNSPECIFIED FORM 305 mg/100 mL
INACTIVE INGREDIENTS: Water

800 mL InterSol Solution Platelet Additive Solution 3 with Twist-off Port

INDICATIONS AND USAGE

6B7800S

12x 800 mL

Rx only
Store at Controlled Room Temperature. Protect from freezing. Avoid excessive heat. Definition of "Controlled Room Temperature":
"A temperature maintained thermostatically that encompasses the usual and customary working environment of 20° to 25°C (68° to 77°F); that results in a mean kinetic temperature calculated to be not more than 25°C; and that allows for excursions between 15°C and 30°C (59° and 86°F) that are experienced in pharmacies, hospitals, and warehouses. Provided the mean kinetic temperature remains in the allowed range, transient spikes up to 40°C are permitted as long as they do not exceed 24 hours ... The mean kinetic temperature is a calculated value that may be used as an isothermal storage temperature that simulates the non isothermal effects of storage temperature variations."
Reference: United States Pharmacopeia, General Notices. United States Pharmacopeial Convention, Inc. 12601 Twinbrook Parkway, Rockville, MD.
Dispose of waste in appropriate biohazard container or according to local regulatory requirements.

Indications and Usage:
InterSol solution is an isotonic solution designed to replace a proportion of the plasma used in the storage of leukoreduced apheresis platelets under standard blood banking conditions. There is no direct therapeutic effect to be expected from the formulation. The solution should never be infused directly into a patient.

InterSol platelets are leukocyte-reduced apheresis platelet concentrates that are stored in a mix of 65% InterSol and 35% plasma, nominal. InterSol platelets prepared within the ranges described in the apheresis system Operator's Manuals may be stored for up to 5 days at 20-24°C, with continuous agitation.

Dosage and Administration:
InterSol solution is to be used with the AMICUS Separator System or the TRIMA ACCEL system. For full instructions on the use of InterSol solution, see the Operator's Manual for the respective platelet collection system.

Dosage Forms and Strengths:
InterSol solution is provided as a 800 mL sterile and non-pyrogenic solution in a non-PVC plastic container with a sterile and non-pyrogenic fluid path. Each 100 mL contains 305 mg Dibasic Sodium Phosphate, Anhydrous, USP; 93 mg Monobasic Sodium Phosphate, Monohydrate, USP; 318 mg Sodium Citrate, Dihydrate, USP; 442 mg Sodium Acetate, Trihydrate, USP; 452 mg Sodium Chloride, USP; Water for Injection, USP quantity sufficient.

Contraindications:
InterSol solution is added to apheresis-derived leukoreduced platelet concentrates after the apheresis procedure is complete. It is not for direct intravenous infusion. There are no known contraindications associated with the use of InterSol solution for the preparation of InterSol platelets.

Warnings and Precautions:

- InterSol solution is NOT FOR DIRECT INTRAVENOUS INFUSION.
- Do not use if particulate matter is present or if the solution is cloudy.
- Do not use if the container is damaged, leaking or if there is any visible sign of deterioration.
- Do not vent.
- Do not reuse. Discard unused or partially used InterSol solution.
- Protect from sharp objects.
- Verify that the InterSol solution has been securely attached to the PAS Connector line to avoid disconnection and leaks.

Adverse Reactions:
InterSol solution is added to leukoreduced platelet concentrates after the apheresis procedure is complete. It is not for direct intravenous infusion. InterSol solution is not expected to cause adverse events other than those normally associated with platelet transfusion.

Drug Abuse / Dependence:
InterSol solution is used as a storage solution for platelet concentrates and has no pharmacological effect.

Overdosage:
InterSol solution is used as a storage solution for platelet concentrates and it is not for direct intravenous infusion.

Description:
InterSol solution is an isotonic solution designed to replace a proportion of the plasma used in the storage of platelets. The solution contains constituents that are naturally occurring components present in many cellular systems: sodium acetate as a nutrient, sodium citrate to prevent platelet clumping and activation, sodium phosphate for buffering and sodium chloride for osmolarity. InterSol solution does not have a pharmacological effect in vivo, but rather acts to provide the appropriate environment and nutrients in lieu of a portion of the plasma normally used for the storage of platelets.

Clinical Pharmacology:
InterSol solution is used as a storage solution for platelet concentrates and it is not for direct intravenous infusion. This solution has no pharmacological effect.

Clinical Studies:

In Vitro Biochemical and Functional Evaluations AMICUS-derived, leukoreduced platelets
InterSol platelet concentrates (n=70) prepared using the AMICUS separator and stored for 5 days showed a median and mean pH value on Day 5 of 7.2 and 7.2 ± 0.1 (range: 6.9-7.5), respectively, with a lower non-parametric 95%/95% tolerance limit of 6.9.

Supplemental in vitro assessments of InterSol platelets and AMICUS-derived leukoreduced platelets stored in 100% plasma are presented in Table 1.

InterSol platelets irradiated (n=18) at either 2500 or 2800 cGray (dependent on site procedures) were compared to non-irradiated InterSol platelets. At the end of storage on Day 5 the platelet yields of the irradiated products were concentrated between 2.5 x 10^11 to 3.5 x 10^11 and included one product with a yield less than2.5 x 10^11 and two products with yields greater than 3.5 x 10^11. In vitro testing is not predictive of in vivo performance, which was not evaluated. Summary statistics are presented in Table 2.

In Vivo Recovery and Survival in Healthy Subjects AMICUS-derived, leukoreduced platelets

In vivo evaluation of InterSol platelets at Day 5 (n=33) compared to a fresh platelet control resulted in a mean percent recovery of 46.4 ± 11.9 percent and 58.0 ± 10.7 percent and mean survival of 5.7 ± 1.4 days and 8.0 ± 1.4 days, respectively. The in vivo data collected were used to calculate the upper limit of a two-sided 95% confidence interval of the mean percent recovery of the algebraic expression (0.66 x Fresh – 5 Day), and of the mean percent survival (days) of the algebraic expression (0.58 x Fresh – 5 Day). The upper bound of the two-sided 95% confidence intervals for recovery and survival on Day 5 was –4.6 and –0.6 respectively and met the requirement of less than 0.

Post-Market Transfusion-Related Adverse Events (AE) Study AMICUS-derived, leukoreduced platelets

An open label, non-randomized, retrospective medical record review study was performed in 6 centers to demonstrate that the overall rate of transfusion-related AEs in patients receiving InterSol Platelet transfusions was not more than double the rate in patients receiving apheresis platelets stored in 100% plasma (Plasma Platelets). The study categorized adverse transfusion reactions according to the definitions outlined by the Biovigilance Component of the National Healthcare Safety Network (NHSN) System. All sites that participated were required to have systems in place to observe transfusion-related AEs and to record when no transfusion-related AE was observed. An independent Clinical Events Committee (CEC) blinded to platelet type and study site adjudicated the reported events.

Patients were prescribed platelet transfusions per each site’s standard practice. The type of platelet unit the patient received was based on the site’s inventory at the time the transfusion was ordered. Site personnel observed the platelet transfusion recipient following their standard procedures. Signs and symptoms of a potential transfusion-related reaction were noted using existing reporting systems. A total of 14,005 transfusions from 6 study sites were included in the final analysis. A total of 4,160 InterSol Platelet transfusions were given to a total of 1,444 patients, and 9,845 Plasma Platelet transfusions were given to 2,202 patients. There were 165 CEC-adjudicated adverse reactions reported. Of those, 23 events were associated with InterSol Platelets and 142 events were associated with Plasma Platelets.

Overall, 1.13% of all transfusions resulted in an AE. The percentage of InterSol Platelet transfusions which led to AEs was 0.55%, while 1.37% of Plasma Platelet transfusions resulted in AEs. The 97.5% upper confidence limit for the relative risk of transfusion-related AE associated with InterSol Platelets relative to Plasma Platelets was 0.66, indicating that the study objective of ruling out a doubling of transfusion-related AEs for InterSol vs. Plasma Platelets was met.

The majority of the 165 CEC-adjudicated reactions were Allergic (n=93) or Febrile Non-Hemolytic Transfusions Reactions (FNHTR, n=56), at 0.66% and 0.40% of total transfusions, respectively. There were allergic reactions associated with 0.29% of InterSol Platelet transfusions and 0.82% of Plasma Platelet transfusions. FNHTR events were associated with 0.17% of InterSol Platelet transfusions and 0.50% of Plasma Platelet transfusions.

No InterSol Platelet transfusion was associated with more than one reaction. Seven (7) Plasma Platelet transfusions (0.07% of total transfusions) were associated with two (2) separate adverse reactions each. Two (2) InterSol Platelet and five (5) Plasma Platelet adverse reactions were classified as severe. All other reactions were classified as non-severe. All adverse reactions were reported with an outcome of “Minor or No Sequelae”.

No adverse safety trends were identified after review of all the AEs by the independent Clinical Events Committee.

In Vitro Biochemical and Functional Evaluations, TRIMA ACCEL-derived, leukoreduced platelets

InterSol platelet concentrates (n = 60) prepared using the Trima Apheresis system and stored for 5 days showed a mean pH value on Day 5 of 7.2 ± 0.1 (range 7.0 – 7.3), with a lower one-sided 95% confidence interval of 0.951.
Supplemental in vitro assessments of TRIMA ACCEL-derived leukoreduced platelets stored in InterSol platelet and 100% plasma are presented in Table 3.

In Vivo Recovery and Survival in Healthy Subjects, TRIMA ACCEL-derived, leukoreduced platelets

In vivo evaluations of TRIMA ACCEL-derived platelets stored in InterSol at Day 5 (n = 24) compared to fresh platelet control resulted in a mean percent recovery of 45.2 ± 12.3 percent and 56.0 ± 13.2 percent and a mean survival of 5.4 ± 1.0 days and 7.9 ± 1.5 days, respectively. The in vivo data collected were used to calculate the upper limit of a one-sided 97.5% confidence interval of the mean percent recovery of the algebraic expression of (0.66 x Fresh – 5 Day) and the mean percent survival (days) of the algebraic expression (0.58 x Fresh – 5 Day). The lower limit of the one-sided 97.5% confidence intervals for recovery and survival on Day 5 was 4.0 and 0.4 respectively and met the requirement of greater than 0.

How Supplied/Storage and Handling:
800 mL sterile solution in a non-PVC plastic container with a sterile, non-pyrogenic fluid path. The InterSol solution container is supplied in a vented plastic overwrap covering that serves as a dust cover for the container. The dust cover is not a sterility barrier and is not an element that defines the expiration date of the InterSol product.

Fresenius Kabi AG
Else-Kröner-Str. 1

61352 Bad Homburg

Germany
Tel.: +49 (0) 61 72 / 686-0
www.fresenius-kabi.com

www.fresenius-kabi.com/us/symbolglossary

For US: 1-800-933-6925

All trademarks shown are property of their respective owners.

© 2025 Fresenius Kabi AG. All rights reserved.

472317814 [B] 2025/03